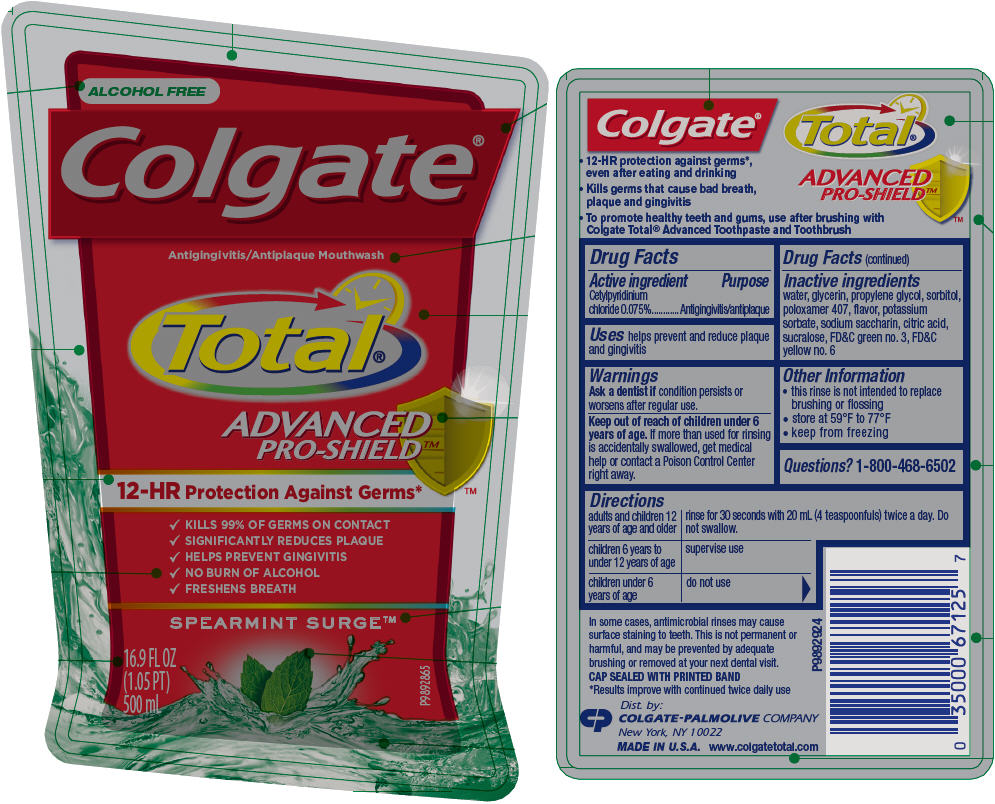 DRUG LABEL: Colgate Total Advanced Pro-Shield Spearmint Surge
NDC: 67659-501 | Form: RINSE
Manufacturer: Team Technologies, Inc
Category: otc | Type: HUMAN OTC DRUG LABEL
Date: 20160517

ACTIVE INGREDIENTS: CETYLPYRIDINIUM CHLORIDE 15 mg/20 mL
INACTIVE INGREDIENTS: WATER; GLYCERIN; PROPYLENE GLYCOL; SORBITOL; POLOXAMER 407; POTASSIUM SORBATE; SACCHARIN SODIUM; LEVOMENTHOL; ANHYDROUS CITRIC ACID; SUCRALOSE; FD&C GREEN NO. 3; FD&C YELLOW NO. 6

Colgate® Total® Advanced Pro-Shield™ Mouthwash Spearmint Surge™

Drug Facts

Active ingredient

Cetylpyridinium chloride 0.075%

Purpose

Antigingivitis/antiplaque

Uses

helps prevent and reduce plaque and gingivitis

Warnings

ASK DOCTOR

Ask a dentist if condition persists or worsens after regular use.

Keep out of reach of children under 6 years of age. If more than used for rinsing is accidentally swallowed, get medical help or contact a Poison Control Center right away.

Directions

adults and children 12 years of age and older | rinse for 30 seconds with 20 mL (4 teaspoonfuls) twice a day. Do not swallow.
children 6 years to under 12 years of age | supervise use
children under 6 years of age | do not use

Inactive ingredients

water, glycerin, propylene glycol, sorbitol, poloxamer 407, flavor, potassium sorbate, sodium saccharin, citric acid, sucralose, FD&C green no. 3, FD&C yellow no. 6

Other Information

- this rinse is not intended to replace brushing or flossing
- store at 59°F to 77°F
- keep from freezing

Questions?

1-800-468-6502

Dist. by:
COLGATE-PALMOLIVE COMPANY
New York, NY 10022

PRINCIPAL DISPLAY PANEL - 500 mL Bottle Label

ALCOHOL FREE

Colgate®

Antigingivitis/Antiplaque Mouthwash

Total®

ADVANCED
PRO-SHIELD ™

12-HR Protection Against Germs*

- KILLS 99% OF GERMS ON CONTACT
- SIGNIFICANTLY REDUCES PLAQUE
- HELPS PREVENT GINGIVITIS
- NO BURN OF ALCOHOL
- FRESHENS BREATH

SPEARMINT SURGE™

16.9 FL OZ
(1.05 PT)
500 mL

P9892865